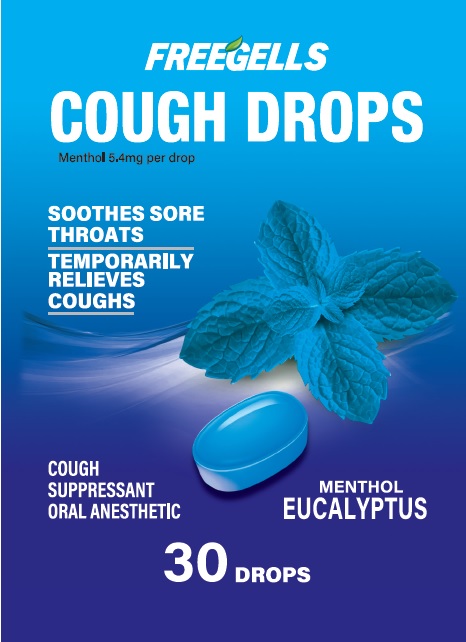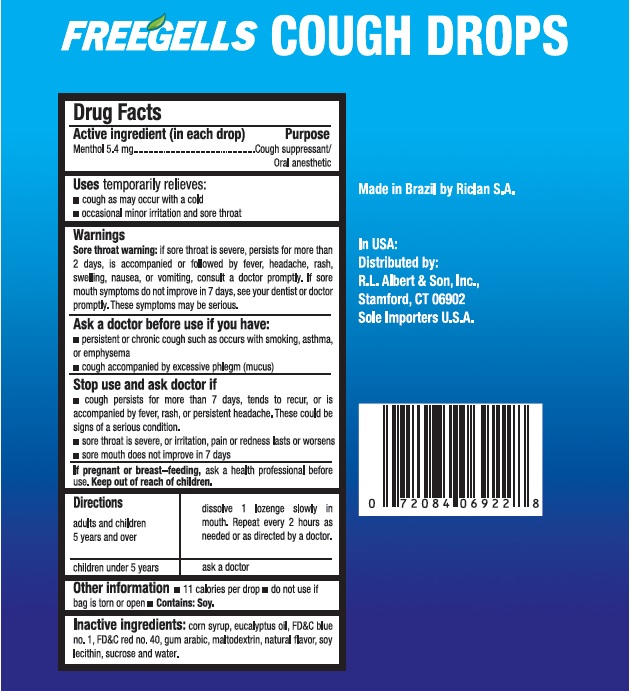 DRUG LABEL: Freegells Cough Drops Menthol 30ct
NDC: 83002-005 | Form: LOZENGE
Manufacturer: R.L. ALBERT & SON, INC
Category: otc | Type: HUMAN OTC DRUG LABEL
Date: 20251024

ACTIVE INGREDIENTS: MENTHOL 5.4 mg/1 1
INACTIVE INGREDIENTS: CORN SYRUP; EUCALYPTOL; LECITHIN, SOYBEAN; FD&C RED NO. 40; FD&C BLUE NO. 1; ACACIA; MALTODEXTRIN; SUCROSE

Drug Facts

Active ingredient

Menthol 5.4 mg

Purpose

Cough Suppressant / Oral anesthetic

Use

Temporarily relieves:

- cough as may occur with a cold
- occasional minor irritation and sore throat

Warning

Sore throat warning: if sore throat is severe, persists for more than 2 days, is accompanied or followed by fever, headache, rash, swelling, nausea, or vomiting, consult a doctor promptly. if sore mouth symptoms do not improve in 7 days, see your dentist or doctor promptly. These symptoms may be serious.

Ask a doctor before use if you have :

- persistent or chronic cough such as occurs with smoking, asthma, or emphysema
- cough accompanined by excessive phlegm (mucus)

stop use and ask doctor if

- cough persists for more than 7 days, tends to recur, or is accompanied by fever, rash, or persistent headache. These could be signs of a serious condition.
- sore throat is severe, or irritation, pain or redness lasts or worsens
- sore mouth does not improve in 7 days

If pregnant or breast-feeding, ask a health professional before use.

Directions

Adults and children 5 years and over

dissolve 1 lozenges slowly in mouth. Repeat every 2 hours as needed or as directed by a doctor

children under 5 years , ask a doctor

Other information

- 11 calories per drop
- do not use if bag is torn or open
- Contains : Soy

Inactive ingredients

Corn Syrup, eucalyptus oil, FD&C blue no. 1, FD&C red no.40, gum Arabic, maltodextrin, natural flavor, soy lecithin, sucrose and water